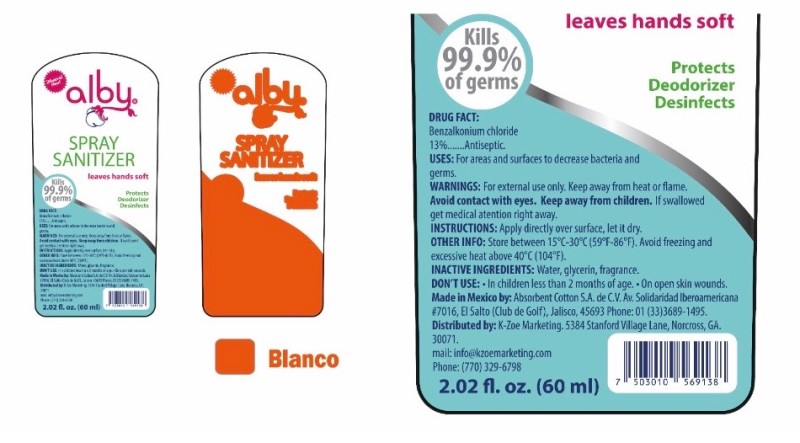 DRUG LABEL: ALBY
NDC: 80686-001 | Form: SPRAY
Manufacturer: K-Zoe Marketing
Category: otc | Type: HUMAN OTC DRUG LABEL
Date: 20201125

ACTIVE INGREDIENTS: BENZALKONIUM CHLORIDE 0.13 g/100 mL
INACTIVE INGREDIENTS: WATER; GLYCERIN

ALBY SPRAY SANITIZER 60ML

Active Ingredient

Benzalkonium Chloride .13%.

Purpuse

Antiseptic.

Uses

For areas and surfaces to decrease bacteria and germs.

Warnings

For external use only. Keep away from heat or flame.

WARNINGS

Avoid contact with eyes

Keep away from children

WARNINGS

If swallowed get medical attention right away.

Instructions

Apply directly over surface, let it dry.

Other Info

Store between 15° - 30°C (59°F - 86°F). Avoid freezing and excessive heat above 40°C (104°F).

Inactive Ingredients

Water, glycerin, fragance.

Don´t use in children less than 2 months of age. On open skin wounds.

INDICATIONS AND USAGE

Spray Sanitizer